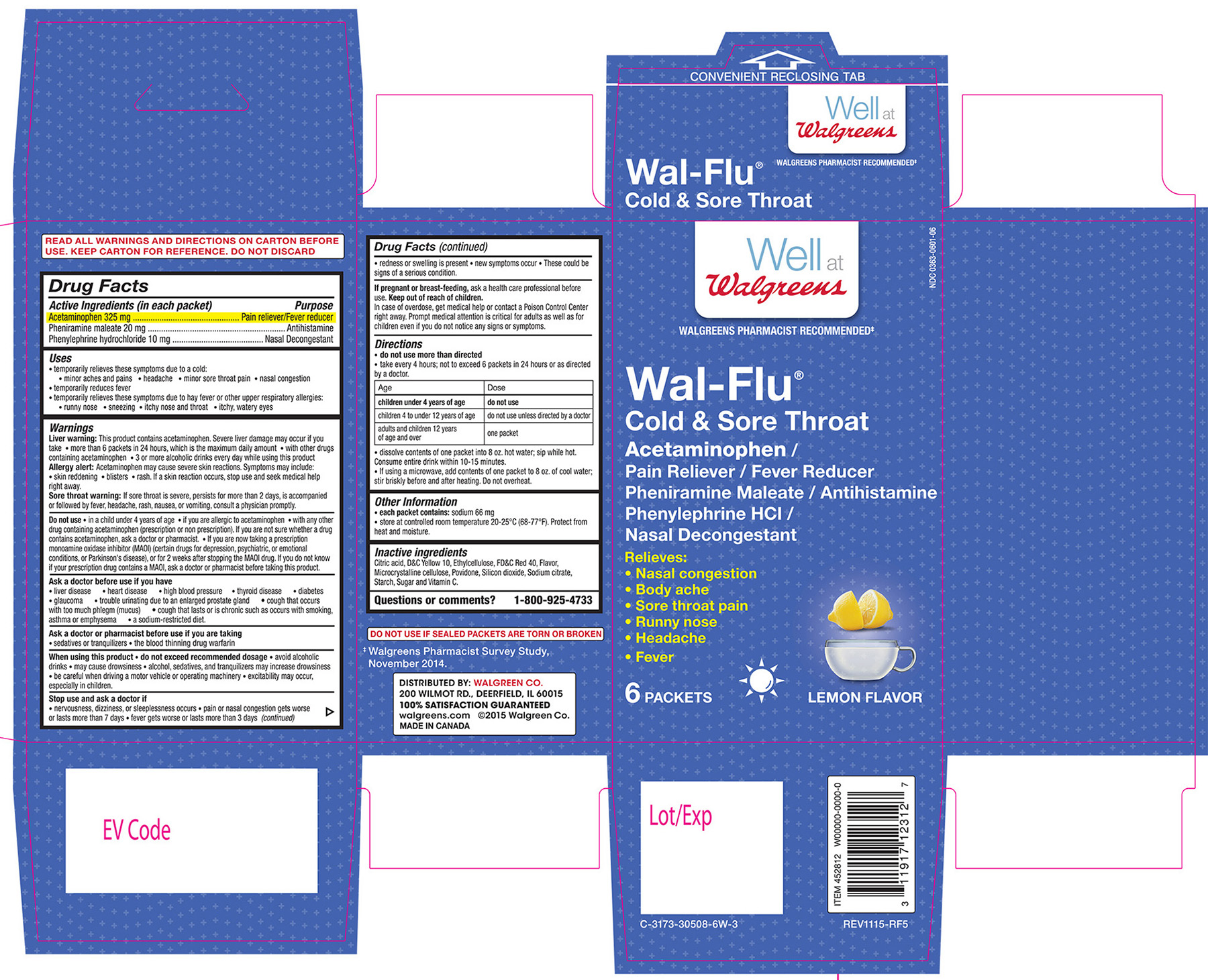 DRUG LABEL: Walgreens Wal-Flu Cold and Sore Throat
NDC: 0363-0601 | Form: GRANULE, FOR SOLUTION
Manufacturer: Walgreen Co.
Category: otc | Type: HUMAN OTC DRUG LABEL
Date: 20160331

ACTIVE INGREDIENTS: ACETAMINOPHEN 325 mg/1 1; PHENIRAMINE MALEATE 20 mg/1 1; PHENYLEPHRINE HYDROCHLORIDE 10 mg/1 1
INACTIVE INGREDIENTS: CITRIC ACID MONOHYDRATE; ETHYLCELLULOSE (100 MPA.S); CELLULOSE, MICROCRYSTALLINE; POVIDONE; SILICON DIOXIDE; SODIUM CITRATE; SUCROSE; ASCORBIC ACID

Walgreens Wal-Flu Cold and Sore Throat Lemon Flavor

Active Ingredients (in each packet) Purpose

Acetaminophen 325 mg...................................Pain reliever/Fever reducer

Pheniramine maleate 20 mg................................................Antihistamine

Phenylephrine hydrochloride 10 mg.............................Nasal decongestant.

Uses

- temporarily relieves these symptoms due to a cold:
- minor aches and pains - headache - minor sore throat pain
- nasal congestion - temporarily reduces fever
- temporarily relieves these symptoms due to hay fever or other upper respiratory allergies:
- runny nose - sneezing - itchy nose and throat - itchy, watery eyes.

Warnings

Liver warning: This product contains acetaminophen. Severe liver damage may occur if you take - more than 6 packets in 24 hours, which is the maximum daily amount - with other drugs containing acetaminophen - 3 or more alcoholic drinks every day while using this product.

Allergy alert: Acetaminophen may cause severe skin reactions. Symptoms may include: - skin reddening - blisters - rash. If a skin reaction occurs, stop use and seek medical help right away.

Sore throat warning: If sore throat is severe, persists for more than 2 days, is accompanied or followed by fever, headache, rash, nausea, or vomiting, consult a physician promptly.

Do not use:

- In a child under 4 years of age.

- If you are allergic to acetaminophen.

- with any other drug containing acetaminophen (prescription and nonprescription). If you are not sure whether a drug contains acetaminophen, ask a doctor or pharmacist.
- if you are now taking a prescription monoamine oxidase inhibitor (MAOI) (certain drugs for depression, psychiatric, or emotional conditions, or Parkinson's disease), or for 2 weeks after stopping the MAOI drug. If you do not know if your prescription drug contains an MAOI, ask a doctor or pharmacist before taking this product.

Ask a doctor before use if you have
- liver disease - heart disease - high blood pressure - thyroid disease - diabetes - glaucoma - trouble urinating due to an enlarged prostate gland - cough that occurs with too much phlegm (mucus) - cough that lasts or is chronic such as occurs with smoking, asthma or emphysema

- a sodium-restricted diet.

Ask a doctor or pharmacist before use if you are taking
- sedatives or tranquilizers

- the blood thinning drug warfarin.

When using this product
- do not exceed recommended dosage
- avoid alcoholic drinks - may cause drowsiness
- alcohol, sedatives, and tranquilizers may increase drowsiness
- be careful when driving a motor vehicle or operating machinery
- excitability may occur, especially in children.

Stop use and ask a doctor if
- nervousness, dizziness, or sleeplessness occur
- pain or nasal congestion gets worse or lasts more than 7 days
- fever gets worse or lasts more than 3 days
- redness or swelling is present
- new symptoms occur

These could be signs of a serious condition.

PREGNANCY OR BREAST FEEDING

If pregnant or breast-feeding, ask a health care professional before use.

Keep out of reach of children.

OVERDOSAGE

Overdose Warning:

In case of overdose, get medical help or contact a poison control center right away. Prompt medical attention is critical for adults as well as for children even if you do not notice any signs or symptoms.

Directions
- do not use more than directed
- take every 4 hours; not to exceed 6 packets in 24 hours or as directed by a doctor

Age | Dose
children under 4 years of age | do not use
children 4 to under 12 years of age | do not use unless directed by a doctor
adults and children 12 years of age and over | one packet

- dissolve contents of one packet in 8 oz. hot water; sip while hot. Consume entire drink within 10-15 minutes.
- If using a microwave, add contents of one packet to 8 oz. of cool water; stir briskly before and after heating. Do not overheat.

Other Information
- each packet contains: sodium 66 mg
- store at controlled room temperature 20-25C (68-77F). Protect from heat and moisture.

INACTIVE INGREDIENT

Citric acid, D and C Yellow 10, Ethylcellulose, FD and C Red 40, Flavor, Microcrystalline cellulose, Povidone, Silicon dioxide, Sodium citrate, Starch, Sugar and Vitamin C.